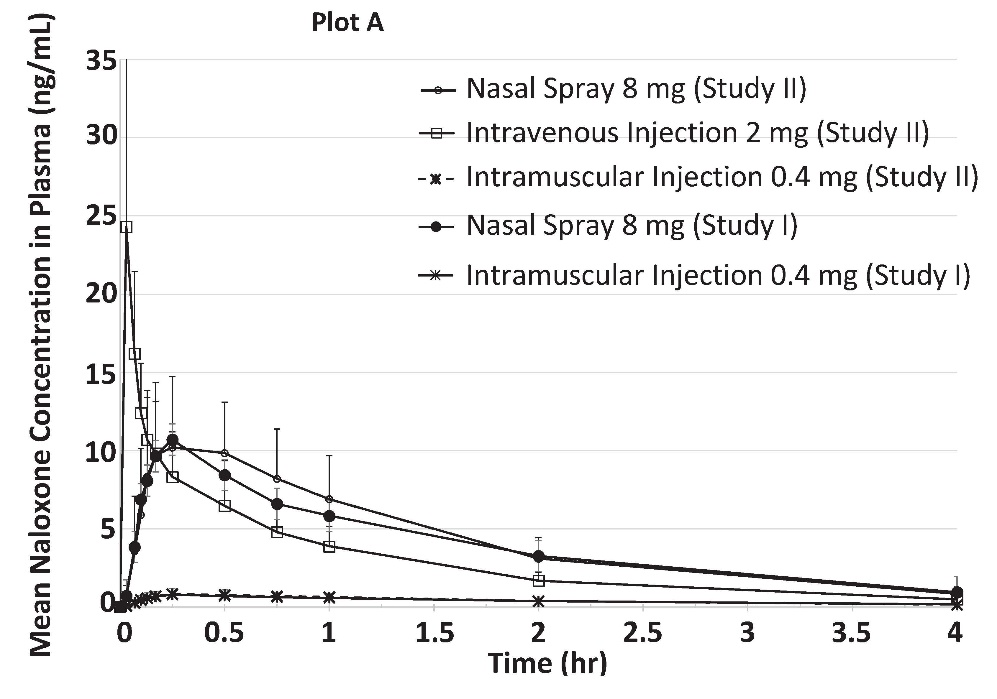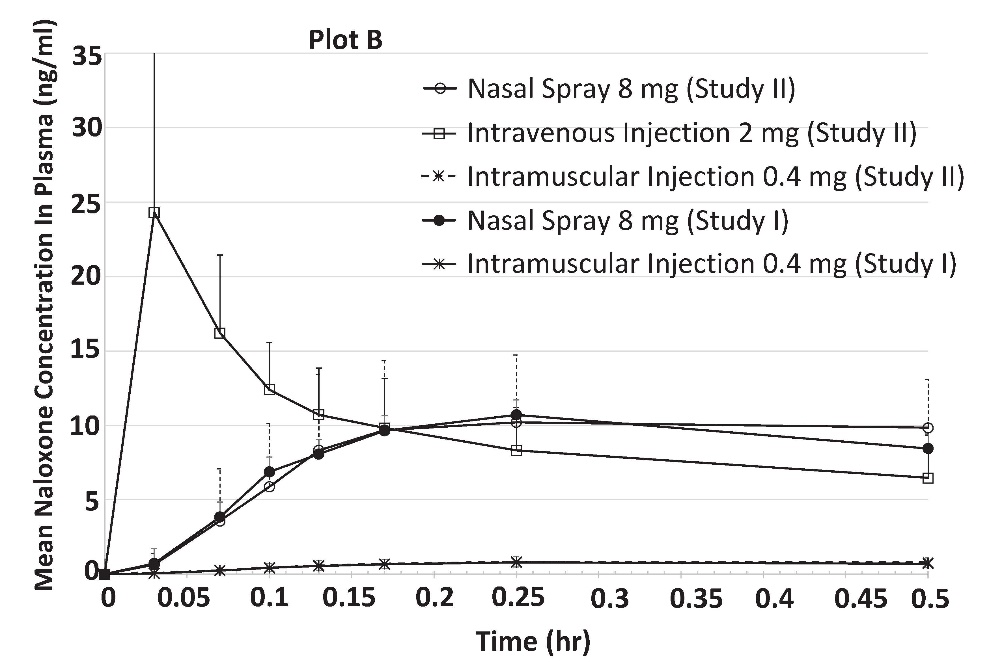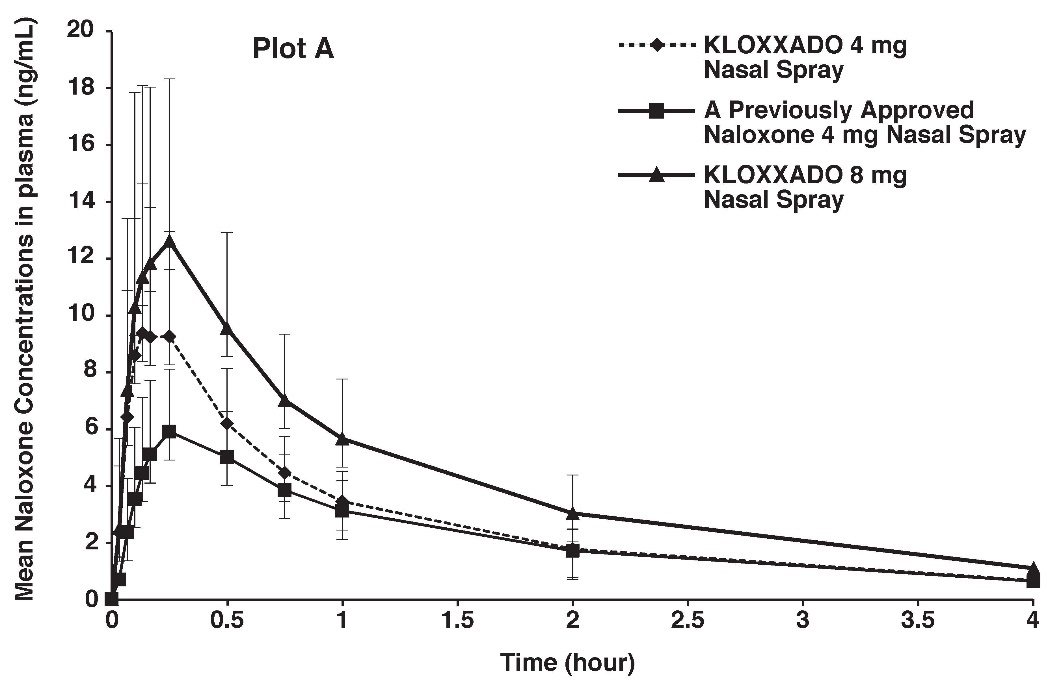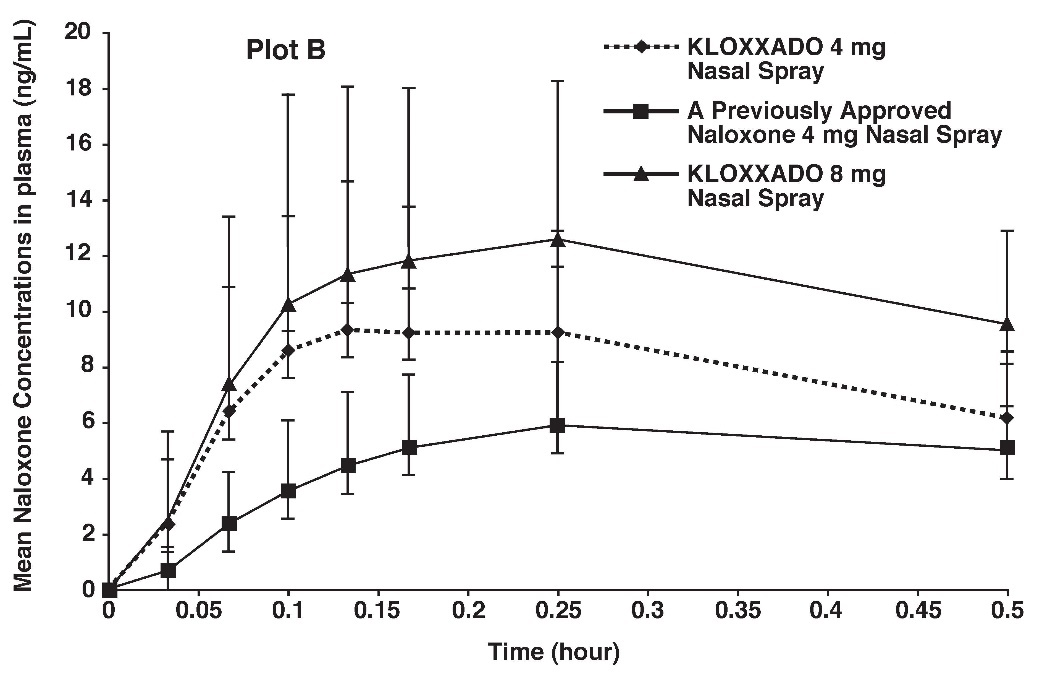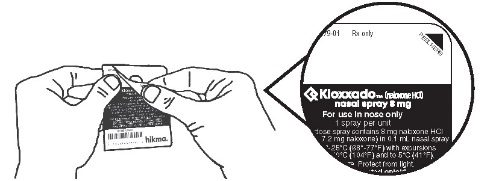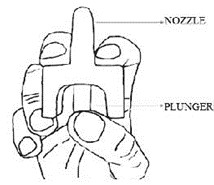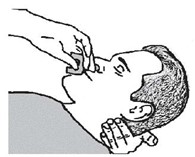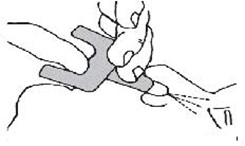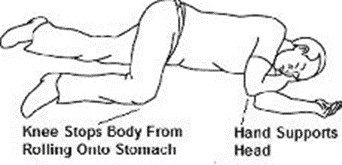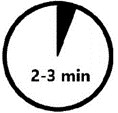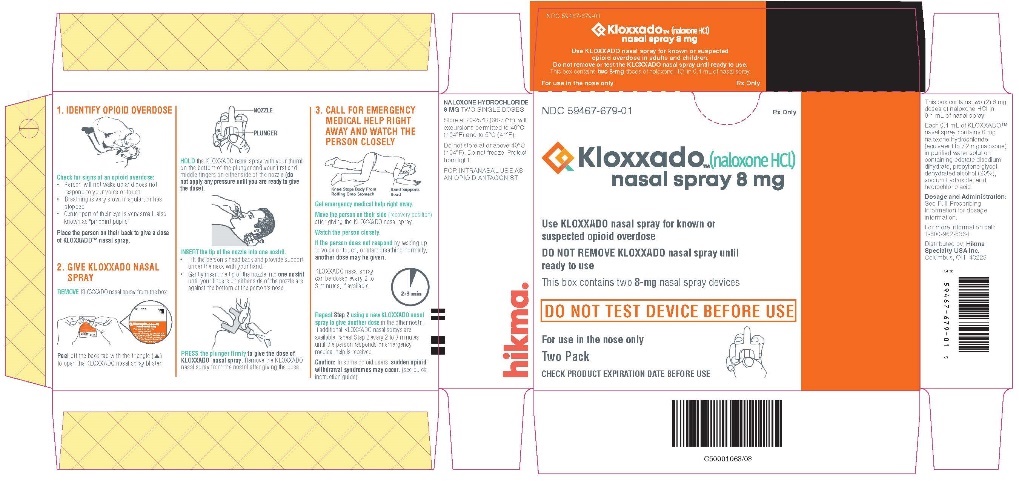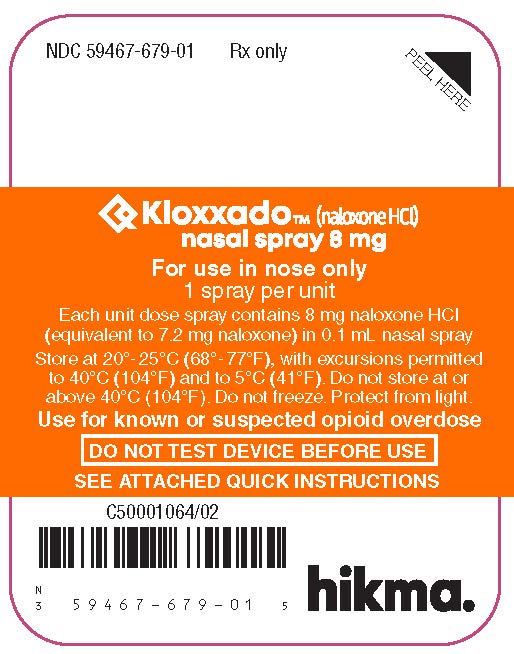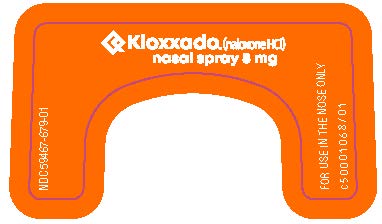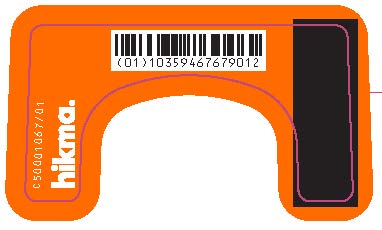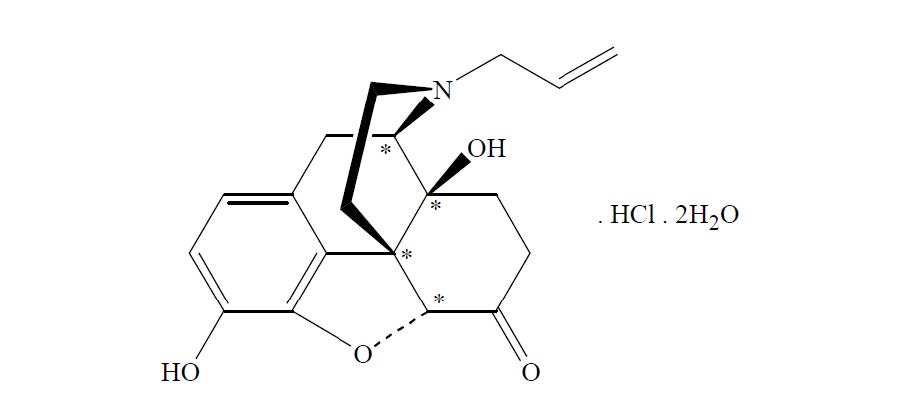 DRUG LABEL: KLOXXADO
NDC: 59467-679 | Form: SPRAY
Manufacturer: Hikma Specialty USA Inc.
Category: prescription | Type: HUMAN PRESCRIPTION DRUG LABEL
Date: 20250825

ACTIVE INGREDIENTS: NALOXONE HYDROCHLORIDE 8 mg/0.1 mL
INACTIVE INGREDIENTS: EDETATE DISODIUM; PROPYLENE GLYCOL; WATER; SODIUM HYDROXIDE; HYDROCHLORIC ACID; ALCOHOL

HIGHLIGHTS OF PRESCRIBING INFORMATION

These highlights do not include all the information needed to use KLOXXADO safely and effectively. See full prescribing information for KLOXXADO.
KLOXXADO® (naloxone hydrochloride) nasal spray
Initial U.S. Approval: 1971

RECENT MAJOR CHANGES

Dosage and Administration (2.1) 08/2025

Warnings and Precautions (5.3) 08/2025

1 INDICATIONS AND USAGE

KLOXXADO is an opioid antagonist indicated for the emergency treatment of known or suspected opioid overdose, as manifested by respiratory and/or central nervous system depression, for adult and pediatric patients. (1)

KLOXXADO is intended for immediate administration as emergency therapy in settings where opioids may be present.

KLOXXADO is not a substitute for emergency medical care. (1)

2 DOSAGE AND ADMINISTRATION

- KLOXXADO is for intranasal use only. (2.1)
- Seek emergency medical care immediately after use. (2.1)
- All approved naloxone hydrochloride products achieve plasma concen- trations effective at reversing the effects of opioid overdose. Comparing products on a nominal mg-for-mg basis may be misleading. (2.1)
- Administer a single spray of KLOXXADO to adult or pediatric patients intranasally into one nostril. (2.2)
- Administer additional doses of KLOXXADO, using a new nasal spray with each dose, if the patient does not respond or responds and then relapses into respiratory depression. Additional doses of KLOXXADO may be given every 2 to 3 minutes until emergency medical assistance arrives. (2.2)
- Additional supportive and/or resuscitative measures may be helpful while awaiting emergency medical assistance. (2.2)

3 DOSAGE FORMS AND STRENGTHS

Nasal spray:

- 8 mg naloxone hydrochloride in 0.1 mL. (3)

4 CONTRAINDICATIONS

Hypersensitivity to naloxone hydrochloride or to any of the other ingredients. (4)

5 WARNINGS AND PRECAUTIONS

- Risk of Recurrent Respiratory and CNS Depression: Due to the duration of action of naloxone relative to the opioid, keep patient under continued surveillance and administer repeat doses of naloxone using a new nasal spray with each dose, as necessary, while awaiting emergency medical assistance. (5.1)
- Risk of Limited Efficacy with Partial Agonists or Mixed Agonist/Antagonists: Reversal of respiratory depression caused by partial agonists or mixed agonist/antagonists, such as buprenorphine and pentazocine, may be incomplete. Larger or repeat doses may be necessary. (5.2)
- Precipitation of Severe Opioid Withdrawal: Use in patients who are opioid dependent may precipitate opioid withdrawal. In neonates, opioid withdrawal may be life-threatening if not recognized and properly treated. Monitor for the development of opioid withdrawal. (5.3)
- Risk of Cardiovascular (CV) Effects: Abrupt postoperative reversal of opioid depression may result in adverse CV effects. These events have primarily occurred in patients who had preexisting CV disorders or received other drugs that may have similar adverse CV effects. Monitor these patients closely in an appropriate healthcare setting after use of naloxone hydrochloride. (5.3)

6 ADVERSE REACTIONS

The following adverse reactions were reported with KLOXXADO in two adult subjects each: abdominal pain, asthenia, dizziness, headache, nasal discomfort, and presyncope. (6.1)

To report SUSPECTED ADVERSE REACTIONS, contact Hikma Specialty USA Inc. at 1-800-962-8364 or FDA at 1-800-FDA-1088 or www.fda.gov/medwatch.

FULL PRESCRIBING INFORMATION

1 INDICATIONS AND USAGE

KLOXXADO is indicated for the emergency treatment of known or suspected opioid overdose, as manifested by respiratory and/or central nervous system depression, for adult and pediatric patients.

KLOXXADO is intended for immediate administration as emergency therapy in settings where opioids may be present.

KLOXXADO is not a substitute for emergency medical care.

2 DOSAGE AND ADMINISTRATION

2.1 Important Dosage and Administration Instructions

- KLOXXADO is for intranasal use only.
- One spray delivers the entire contents of the drug product.
- All approved naloxone hydrochloride products achieve plasma concentrations that have been shown to be efficacious in reversing the effects of opioid overdose. Comparing different products on a nominal mg-for-mg basis may be misleading [see Clinical Pharmacology (12.3)].
- The device is ready to use. Do not prime or test prior to administration.
- Do not attempt to reuse KLOXXADO. Each KLOXXADO contains a single dose of naloxone and cannot be reused.
- Because suspected opioid overdose is usually managed by someone other than the patient, instruct the prescription recipient to inform those around them about the presence of KLOXXADO and the Instructions for Use.
Instruct the patient or caregiver to read the Instructions for Use at the time they receive a prescription for KLOXXADO. Emphasize the following instructions to the patient or caregiver.
- Administer KLOXXADO as quickly as possible because prolonged respiratory depression may result in damage to the central nervous system or death.
- Always seek immediate emergency medical assistance after the first dose of KLOXXADO has been administered in the event of a suspected, potentially life-threatening opioid emergency because the duration of action of most opioids exceeds that of naloxone hydrochloride. Keep the patient under continued surveillance and administer repeated doses of KLOXXADO, as necessary, until emergency personnel arrive [see Warnings and Precautions (5.1)].
- Administer KLOXXADO according to the printed instructions on the carton and the Instructions for Use.
- Place the patient in the supine position. Prior to administration, be sure the device nozzle is inserted in either nostril of the patient and provide support to the back of the neck to allow the head to tilt back. Do not prime or test the device prior to administration.
- To administer the dose, press firmly on the device plunger and remove the device nozzle from the nostril after use. Place the patient in recovery position by turning him/her onto their side as shown in the Instructions for Use and call for emergency medical assistance immediately after the first dose of KLOXXADO.
- Administer additional doses of KLOXXADO, using a new nasal spray, every 2 to 3 minutes as needed if the patient does not respond or responds and then relapses into respiratory depression. Administer KLOXXADO in alternate nostrils with each dose [see Dosing and Administration (2.2)].

2.2 Dosing in Adult and Pediatric Patients

Initial Dosing

KLOXXADO nasal spray, 8 mg

The recommended initial dose of KLOXXADO in adult and pediatric patients is one spray delivered by intranasal administration into one nostril, which delivers 8 mg of naloxone hydrochloride to adult or pediatric patients.

Repeat Dosing

Seek emergency medical assistance as soon as possible, after administering the first dose of KLOXXADO.

If the desired response is not obtained after 2 or 3 minutes, administer an additional dose using a new KLOXXADO in alternate nostril. If there is still no response and additional doses are available, administer additional doses of KLOXXADO every 2 to 3 minutes, alternating nostrils and using a new KLOXXADO, until emergency medical assistance arrives. The requirement for repeat doses of KLOXXADO depends upon the amount, type, and route of administration of the opioid being antagonized.

If the patient responds to KLOXXADO and subsequently relapses back into respiratory depression before emergency assistance arrives, administer an additional dose using a new KLOXXADO, in the opposite nostril, and continue surveillance of the patient.

Additional supportive and/or resuscitative measures may be helpful while awaiting emergency medical assistance.

Reversal of respiratory depression by partial agonists or mixed agonist/antagonists, such as buprenorphine and pentazocine, may be incomplete and require repeated administration of KLOXXADO using a new nasal spray
[see Warnings and Precautions (5.2)].

3 DOSAGE FORMS AND STRENGTHS

Nasal spray: a clear, colorless to yellow solution filled into a clear glass vial, stoppered, and fitted with a unit-dose nasal spray device containing 8 mg of naloxone hydrochloride (equivalent to 7.2 mg naloxone) in 0.1 mL of spray.

4 CONTRAINDICATIONS

KLOXXADO is contraindicated in patients known to be hypersensitive to naloxone hydrochloride or to any of the other ingredients in KLOXXADO.

5 WARNINGS AND PRECAUTIONS

5.1 Risk of Recurrent Respiratory and Central Nervous System Depression

The duration of action of most opioids may exceed that of KLOXXADO resulting in a return of respiratory and/or central nervous system depression after an initial improvement in symptoms. Therefore, it is necessary to seek emergency assistance immediately after administration of the first dose of KLOXXADO and to keep the patient under continued surveillance. Administer additional doses of KLOXXADO if the patient is not adequately responding or responds and then relapses back into respiratory depression, as necessary [see Dosage and Administration (2.2)]. Additional supportive and/or resuscitative measure may be helpful while awaiting emergency medical assistance.

5.2 Risk of Limited Efficacy with Partial Agonists or Mixed Agonist/Antagonists

Reversal of respiratory depression by partial agonists or mixed/antagonists such as buprenorphine and pentazocine may be incomplete. Larger or repeat doses of naloxone hydrochloride may be required to antagonize buprenorphine because the latter has a long duration of action due to its slow rate of binding and subsequent slow dissociation from the opioid receptor [see Dosage and Administration (2.2)]. Buprenorphine antagonism is characterized by a gradual onset of the reversal effects and a decreased duration of action of the normally prolonged respiratory depression.

5.3 Precipitation of Severe Opioid Withdrawal

The use of KLOXXADO in patients who are opioid-dependent may precipitate opioid withdrawal; the risk and severity of withdrawal increases as naloxone exposure increases. Opioid withdrawal is characterized by the following signs and symptoms: body aches, diarrhea, tachycardia, fever, runny nose, sneezing, piloerection, sweating, yawning, nausea or vomiting, nervousness, restlessness or irritability, shivering or trembling, abdominal cramps, weakness, and increased blood pressure. In neonates, opioid withdrawal may be life-threatening if not recognized and properly treated and may include the following signs and symptoms: convulsion, excessive crying, and hyperactive reflexes. Monitor the patient for the development of the signs and symptoms of opioid withdrawal.

Abrupt postoperative reversal of opioid depression after using naloxone hydrochloride may result in nausea, vomiting, sweating, tremulousness, tachycardia, hypotension, hypertension, seizures, ventricular tachycardia and fibrillation, pulmonary edema, and cardiac arrest. Death, coma, and encephalopathy have been reported as sequelae of these events. These events have primarily occurred in patients who had pre-existing cardiovascular disorders or received other drugs that may have similar adverse cardiovascular effects. Monitor patients with pre-existing cardiac disease or patients who have received medications with potential adverse cardiovascular effects for hypotension, ventricular tachycardia or fibrillation, and pulmonary edema in an appropriate healthcare setting. It has been suggested that the pathogenesis of pulmonary edema associated with the use of naloxone hydrochloride is similar to neurogenic pulmonary edema, i.e., a centrally mediated massive catecholamine response leading to a dramatic shift of blood volume into the pulmonary vascular bed resulting in increased hydrostatic pressures.

There may be clinical settings, particularly the postpartum period in neonates with known or suspected exposure to maternal opioid use, where it is preferable to avoid the abrupt precipitation of opioid withdrawal symptoms. In these settings, consider use of an alternative, naloxone-containing product that can be titrated to effect and, where applicable, dosed according to weight [see Use in Specific Population (8.4)].

6 ADVERSE REACTIONS

The following serious adverse reactions are discussed elsewhere in the labeling:

- Recurrent Respiratory and Central Nervous System Depression [see Warnings and Precautions (5.1)]
- Precipitation of Severe Opioid Withdrawal [see Warnings and Precautions (5.3)]

6.1 Clinical Trials Experience

Because clinical studies are conducted under widely varying conditions, adverse reaction rates observed in the clinical studies of a drug cannot be directly compared to the rates in the clinical studies of another drug and may not reflect the rates observed in practice.

KLOXXADO nasal spray, 4 mg

No adverse events were reported in a pharmacokinetic study of 72 healthy adult volunteers exposed to one spray of 4 mg KLOXXADO nasal spray in one nostril.

KLOXXADO nasal spray, 8 mg

In two pharmacokinetic studies a total of 47 healthy adult volunteers were exposed to a single dose of KLOXXADO nasal spray 8 mg, one spray in one nostril. The following adverse reactions were reported in two subjects each: abdominal pain, asthenia, dizziness, headache, nasal discomfort, and presyncope. On local tissue assessments for nasal irritation, signs of nasal inflammation and nasal congestion were observed.

6.2 Postmarketing Experience

The following adverse events have been identified during the post-approval use of naloxone hydrochloride injection in the postoperative setting. Because these reactions are reported voluntarily from a population of uncertain size, it is not always possible to reliably estimate their frequency or establish a causal relationship to drug exposure: hypotension, hypertension, ventricular tachycardia and fibrillation, dyspnea, pulmonary edema, and cardiac arrest. Death, coma, and encephalopathy have been reported as sequelae of these events. Excessive doses of naloxone hydrochloride in postoperative patients have resulted in significant reversal of analgesia and have caused agitation.

Abrupt reversal of opioid effects in persons who were physically dependent on opioids has precipitated an acute withdrawal syndrome. Signs and symptoms have included: body aches, fever, sweating, runny nose, sneezing, piloerection, yawning, weakness, shivering or trembling, nervousness, restlessness or irritability, diarrhea, nausea or vomiting, abdominal cramps, increased blood pressure, tachycardia. In some patients, there was aggressive behavior upon abrupt reversal of an opioid overdose. In the neonate, opioid withdrawal has included: convulsions, excessive crying, hyperactive reflexes [see Warnings and Precautions (5.3)].

The following most frequently reported events (in decreasing frequency) have been identified primarily during post-approval use of naloxone hydrochloride (all routes of administration): withdrawal syndrome, vomiting, nonresponsiveness to stimuli, drug ineffective, agitation, somnolence, and loss of consciousness.

8 USE IN SPECIFIC POPULATIONS

8.1 Pregnancy

Risk Summary

Available data from retrospective cohort studies on naloxone use in pregnant women have not identified a drug-associated risk of major birth defects, miscarriage, or adverse maternal or fetal outcomes. Naloxone may precipitate opioid withdrawal in the pregnant woman and fetus [see Warnings and Precautions (5.3) and Clinical Considerations]. In animal reproduction studies, no embryotoxic or teratogenic effects were observed in mice and rats treated with naloxone hydrochloride during the period of organogenesis at doses equivalent to 3-times and 6-times, respectively, a human dose of 16 mg (see Data).

The estimated background risk of major birth defects and miscarriage for the indicated population(s) is unknown. All pregnancies have a background risk of birth defect, loss, or other adverse outcomes. In the U.S. general population, the estimated background risk of major birth defects and miscarriage in clinically recognized pregnancies is 2 to 4% and 15 to 20%, respectively.

Clinical Considerations

Maternal and Fetal/Neonatal Adverse Reactions

Naloxone hydrochloride crosses the placenta, and may precipitate withdrawal in the fetus, as well as in the opioid-dependent mother [see Warnings and Precautions (5.3)]. The fetus should be evaluated for signs of distress after KLOXXADO is used. Careful monitoring is needed until the fetus and mother are stabilized.

Data

Animal Data

Naloxone hydrochloride was administered during organogenesis to mice and rats at doses 3-times and 6-times, respectively, a human dose of 16 mg based on body surface area comparison. These studies demonstrated no embryotoxic or teratogenic effects due to naloxone hydrochloride.

8.2 Lactation

Risk Summary

There is no information regarding the presence of naloxone in human milk, the effects of naloxone on the breastfed infant or on milk production. Studies in nursing mothers have shown that naloxone does not affect prolactin or oxytocin hormone levels. Naloxone is minimally orally available and is unlikely to affect the breastfed infant.

8.4 Pediatric Use

The safety and effectiveness of KLOXXADO have been established in pediatric patients of all ages for known or suspected opioid overdose as manifested by respiratory and/or central nervous system depression. Use of naloxone hydrochloride in pediatric patients is supported by evidence from adult bioavailability studies with additional evidence from the reported safe and effective use of other naloxone hydrochloride products. No pediatric studies were conducted for KLOXXADO.

Absorption of naloxone hydrochloride following intranasal administration in pediatric patients may be erratic or delayed. Even when the opiate-intoxicated pediatric patient responds appropriately to naloxone hydrochloride, he/she must be carefully monitored for at least 24 hours, as a relapse may occur as naloxone hydrochloride is metabolized.

In opioid-dependent pediatric patients, (including neonates), administration of naloxone hydrochloride may result in an abrupt and complete reversal of opioid effects, precipitating an acute opioid withdrawal syndrome. There may be clinical settings, particularly the postpartum period in neonates with known or suspected exposure to maternal opioid use, where it is preferable to avoid the abrupt precipitation of opioid withdrawal symptoms. Unlike acute opioid withdrawal in adults, acute opioid withdrawal in neonates manifesting as seizures may be life-threatening if not recognized and properly treated. Other signs and symptoms in neonates may include excessive crying and hyperactive reflexes. In these settings where it may be preferable to avoid the abrupt precipitation of acute opioid withdrawal symptoms, consider use of an alternative, naloxone hydrochloride product that can be dosed according to weight and titrated to effect [see Warnings and Precautions (5.3)].

Also, in situations where the primary concern is for infants at risk for opioid overdose, consider whether the availability of alternate naloxone-containing products may be better suited than KLOXXADO.

Juvenile Animal Study

In a juvenile animal study, male and female juvenile rats were administered a single intranasal dose of saline, vehicle consisting of 20% alcohol and 5% propylene glycol, or naloxone (123 mg/kg, 185 mg/kg, and 246 mg/kg) on postnatal day 7 (PND 7). There were no test article-related findings on sexual maturation, neuroapoptosis, or on a limited number of neurocognitive endpoints which included social interactions as well as learning and memory. The no-effect dose level for neurodevelopmental toxicity was the high dose tested, which is 2.7-times a neonate dose based on body surface area comparison and a neonate weight of 2.5 kg.

8.5 Geriatric Use

Clinical studies of KLOXXADO did not include sufficient numbers of subjects aged 65 and over to determine whether they respond differently from younger subjects. Other reported clinical experience has not identified differences in responses between the elderly and younger patients. In general, dose selection for an elderly patient should be cautious, usually starting at the low end of the dosing range, reflecting the greater frequency of decreased hepatic, renal, or cardiac function, and of concomitant disease or other drug therapy.

11 DESCRIPTION

KLOXXADO (naloxone hydrochloride) nasal spray contains the active moiety naloxone, an opioid antagonist, in the form of hydrochloride salt. The chemical name of Naloxone hydrochloride dihydrate is 17-Allyl-4,5α-epoxy-3,14-dihydroxymorphinan-6-one hydrochloride dihydrate. It has the molecular weight of 399.87 g/mol.

Naloxone hydrochloride dihydrate molecular formula is C19H21NO4·HCl·2H2O, and it has the following chemical structure, as shown below.

Naloxone hydrochloride occurs as a white to slightly off-white powder, and is soluble in water, in dilute acids, and in strong alkali; slightly soluble in alcohol; practically insoluble in ether and in chloroform.

KLOXXADO (naloxone hydrochloride) nasal spray is supplied in a pre-filled, single-dose intranasal spray. Each spray or 0.1 mL of KLOXXADO (naloxone hydrochloride) nasal spray contains 8 mg of naloxone hydrochloride (equivalent to 8.79 mg of naloxone hydrochloride dihydrate, USP or 7.2 mg naloxone). Inactive ingredients are dehydrated alcohol
(8 mg strength: 20% (w/w)), edetate disodium dihydrate, USP, propylene glycol, USP, and sodium hydroxide, NF and hydrochloric acid, NF as pH adjusters, in purified water, USP. The pH range for KLOXXADO (naloxone hydrochloride) nasal spray is from 4.0 to 5.5.

12 CLINICAL PHARMACOLOGY

12.1 Mechanism of Action

Naloxone hydrochloride is an opioid antagonist that antagonizes opioid effects by competing for the same receptor sites. Administration of naloxone hydrochloride reverses the effects of opioids, including respiratory depression, sedation and hypotension. It can also reverse the psychotomimetic and dysphoric effects of agonist-antagonists such as pentazocine.

12.2 Pharmacodynamics

When naloxone hydrochloride is administered intravenously, the onset of action is generally apparent within two minutes. The time to onset of action is shorter for intravenous compared to subcutaneous or intramuscular routes of administration. The duration of action is dependent upon the dose and route of administration of naloxone hydrochloride.

12.3 Pharmacokinetics

In a pharmacokinetic study in up to 72 healthy adult volunteers under fasting conditions, the bioavailability (BA) of a single 4 mg dose (one spray) of KLOXXADO was compared to a single 8 mg nasal dose of KLOXXADO and a single
4 mg nasal dose of a previously approved naloxone nasal spray. Naloxone plasma concentration versus time profiles are shown in Figure 1. The pharmacokinetic parameters of naloxone are summarized in Table 1.

Figure 1. Mean ± SD Plasma Concentration Time Profiles of Naloxone Following a Single Dose of Kloxxado nasal spray 4 mg versus Kloxxado 8 mg nasal spray, and a Previously Approved naloxone nasal spray 4 mg in Healthy Subjects (A: 0-4h and B: 0-30 min)

Kloxxado nasal spray 4 mg, Kloxxado nasal spray 8 mg, and a Previously Approved Naloxone Nasal Spray 4 mg Administration in Healthy Subjects

Kloxxado nasal spray 4 mg, Kloxxado nasal spray 8 mg, and a Previously Approved Naloxone Nasal Spray 4 mg Administration in Healthy Subjects
Parameter | Kloxxado Nasal Spray 4 mg | Previously Approved Naloxone Nasal Spray 4 mg | Kloxxado Nasal Spray 8 mg
N | 71 [N=71 due to withdrawal.] | 70 [N=70 due to withdrawal.] | 70
Tmax(h) [Tmax reported as median (minimum – maximum).] | 0.17 (0.07-0.50) | 0.25 (0.13-1.00) | 0.25 (0.07-1.00)
Cmax (ng/mL) | 11.11 (41.74) | 6.56 (35.87) | 14.41 (47.17)
AUClast (ngh/mL) | 12.31 (31.61) | 10.14 (35.44) | 19.57 (35.39)
AUC0inf (ngh/mL) | 12.57 (30.63) | 10.41 (33.82) | 19.81 (34.73)
T1/2 (h) | 1.27 (26.32) | 1.30 (26.22) | 1.56 (126.82)

In two pharmacokinetic studies in up to 24 healthy adult volunteers for each study, the bioavailability (BA) of a single
8 mg dose (one spray) of KLOXXADO was compared to a single 0.4 mg intramuscular dose and a single 2 mg intravenous dose of naloxone. Naloxone plasma concentration versus time profiles are shown in Figure 2. The pharmacokinetic parameters of naloxone are summarized in Table 2.

Figure 2. Mean ± SD Plasma Concentration-Time Profiles of Naloxone Following A Single Dose of Intranasal versus Intramuscular/Intravenous Administration in Healthy Subjects. (A: 0-4 h and B: 0-30 min.)

Table 2. Mean (CV%) Plasma Pharmacokinetic Parameters of Naloxone Following a Single Dose of Intranasal and Intramuscular/Intravenous Administration in Healthy Subjects

Parameter | KLOXXADO 8 mg |  | Intramuscular Injection 0.4 mg |  | Intravenous Injection 2 mg
Study | Study I | Study II | Study I | Study II | Study II
N | 24 | 23 [N=23 due to one subject withdrawal.] | 24 | 23 | 24
Tmax(h) [Tmax reported as median (minimum – maximum).] | 0.25 (0.10 – 1.00) | 0.25 (0.10 – 1.00) | 0.25 (0.13 – 1.00) | 0.25 (0.10 – 1.00) | NA
Cmax (ng/mL) | 12.3 (55.4) | 12.8 (37.0) | 0.876 (36.7) | 0.910 (36.8) | 26.2 (82.4) [Cmax of Intravenous Injection 2 mg was observed value from the first sampling time of 2 minutes post-dose.]
AUClast (ng•h/mL) | 18.0 (29.6) | 18.4 (33.4) | 1.82 (24.0) | 1.87 (24.7) | 12.7 (27.6)
AUC0-inf (ng•h/mL) | 16.7 (31.9) [N=15] | 19.0 (32.7) [N=19] | 1.94 (20.9) [N=22 for AUC0-inf and t1/2] | 1.95 (21.9) | 12.8 (27.5)
t1/2 (h) | 2.69 (69.9) | 1.76 (39.7) | 1.41 (20.0) | 1.40 (38.9) | 1.22 (16.4)
Dose normalized Relative BA (%) vs IM Injection | 41.6 | 47.4 | 100 | 100 | NA
Dose normalized Absolute BA (%) vs IV Injection | NA | 36.6 | NA | 77.2 | 100
NA= Not applicable

Absorption

The median Tmax for naloxone following administration of a single dose of 4 mg Kloxxado nasal spray, a previously approved naloxone nasal spray 4 mg, and Kloxxado nasal spray 8 mg were 0.17 hour, 0.25 hour, and 0.25 hour, respectively. The median Tmax (15 min) for naloxone following administration of a single dose of 8 mg KLOXXADO nasal spray was the same as following administration of a single intramuscular dose of 0.4 mg naloxone hydrochloride.

The relative bioavailability of naloxone following administration of a single dose 4 mg Kloxxado nasal spray was 122% as compared to following administration of a single intranasal dose of a previously approved naloxone nasal spray 4 mg. The relative bioavailability of naloxone following administration of a single dose of 4 mg Kloxxado nasal spray was 65% as compared to following administration of a single intranasal dose of 8 mg Kloxxado. The dose normalized relative bioavailability of naloxone following administration of a single dose of 8 mg KLOXXADO was 42 to 47% as compared to following administration of a single intramuscular dose of 0.4 mg naloxone hydrochloride. The absolute bioavailability of naloxone following administration of a single dose of 8 mg KLOXXADO nasal spray was 37% as compared to following administration of a single intravenous dose of 2 mg naloxone hydrochloride.

Distribution

Following parenteral administration, naloxone is distributed in the body and readily crosses the placenta. Plasma protein binding occurs but is relatively weak. Plasma albumin is the major binding constitute, but significant binding of naloxone also occurs to plasma constituents other than albumin. It is not known whether naloxone is excreted into human milk.

Elimination

Following a single intranasal administration of Kloxxado nasal spray 4 mg, the mean half-life (t1/2) of naloxone in plasma was approximately 1.27 (26.32% CV) hours. The mean t1/2 was 1.30 (26.22% CV) hours for a 4 mg intranasal administration of a previously approved naloxone nasal spray and 1.56 (126.82% CV) hours for an 8 mg Kloxxado intranasal administration. Following a single intranasal administration of 8 mg KLOXXADO, the mean half-life (t1/2) of naloxone in plasma was 1.8 (39.7% CV) to 2.7 (69.6% CV) hours. The mean t1/2 was 1.4 (38.9% CV) to 1.4 (20.0% CV) hours for a 0.4 mg naloxone hydrochloride intramuscular injection and 1.2 (16.4% CV) hours for a 2 mg naloxone hydrochloride intravenous injection. In a neonatal study of naloxone hydrochloride the mean (±SD) plasma half-life was observed to be 3.1 ± 0.5 hours.

Metabolism

Naloxone hydrochloride is metabolized in the liver, primarily by glucuronide conjugation, with naloxone-3-glucoronide as the major metabolite.

Excretion

After an oral or intravenous dose, about 25 to 40% of naloxone is excreted as metabolites in urine within 6 hours, about 50% in 24 hours, and 60 to 70% in 72 hours.

13 NONCLINICAL TOXICOLOGY

13.1 Carcinogenesis, Mutagenesis, Impairment of Fertility

Carcinogenesis

Studies in animals to assess the carcinogenic potential of naloxone have not been conducted.

Mutagenesis

Naloxone was weakly positive in the Ames mutagenicity and in the in vitro human lymphocyte chromosome aberration test but was negative in the in vitro Chinese hamster V79 cell HGPRT mutagenicity assay and in the in vivo rat bone marrow chromosome aberration study.

Impairment of Fertility

Reproduction studies conducted in mice and rats at doses 3-times and 6-times, respectively, a human dose of 16 mg based on body surface area comparison, demonstrated no adverse effects on fertility of naloxone hydrochloride.

16 HOW SUPPLIED/STORAGE AND HANDLING

KLOXXADO (naloxone hydrochloride) nasal spray is a clear, colorless to yellow solution supplied in a single-dose spray device that consists of a stoppered glass vial encased in a container holder fitted with a spray actuator, cannula, and spray pin. It delivers a single dose of 8 mg of naloxone hydrochloride (equivalent to 7.2 mg naloxone) in 0.1 mL.

Each KLOXXADO carton contains two individual blisters sealed with a paper backing with a “peel off” feature. The carton contains abbreviated instructions-for-use printed on the back. In addition, a quick instructions leaflet is attached to the bottom of each individual blister.

KLOXXADO nasal spray, 8 mg

1 Carton containing two nasal spray devices: NDC# 59467-679-01

Not made with natural rubber latex.

Storage and Handling

Store KLOXXADO in the blister and cartons provided.

Store at 20ºC to 25ºC (68ºF to 77ºF), with excursions permitted to 40°C (104°F) and to 5°C (41°F). Do not store at or above 40°C (104°F). Do not freeze. Protect from light.

KLOXXADO freezes at temperatures below -15°C (5°F). If this happens, the device will not spray. If KLOXXADO is frozen and is needed in an emergency, do NOT wait for KLOXXADO to thaw. Get emergency medical help right away. However, KLOXXADO may be thawed by allowing it to sit at room temperature for 15 minutes, and it may still be used if it has been thawed after being previously frozen.

17 PATIENT COUNSELING INFORMATION

Advise the patient and family members or caregivers to read the FDA-approved patient labeling (Patient Information and Instructions for Use).

Recognition of Opioid Overdose

Inform patients and their family members or caregivers about how to recognize the signs and symptoms of an opioid overdose such as the following:

- Extreme somnolence – inability to awaken a patient verbally or upon a firm sternal rub.
- Respiratory depression – this can range from slow or shallow respiration to no respiration in a patient who is unarousable.
- Other signs and symptoms that may accompany somnolence and respiratory depression include the following:
- Miosis
- Bradycardia and/or hypotension

Risk of Recurrent Respiratory and Central Nervous System Depression

Instruct patients and their family members or caregivers that, because the duration of action of most opioids may exceed that of KLOXXADO, they must seek immediate emergency medical assistance after the first dose of KLOXXADO and keep the patient under continued surveillance [see Dosage and Administration (2.2), Warnings and Precautions (5.3)].

Limited Efficacy for/with Partial Agonists or Mixed Agonist/Antagonists

Instruct patients and their family members or caregivers that the reversal of respiratory depression caused by partial agonists or mixed agonist/antagonists, such as buprenorphine and pentazocine, may be incomplete and may require higher doses of naloxone hydrochloride or repeated administration of KLOXXADO, using a new nasal spray each time [see Dosage and Administration (2.2), Warnings and Precautions (5.2)].

Precipitation of Severe Opioid Withdrawal

Instruct patients and their family members or caregivers that the use of KLOXXADO in patients who are opioid dependent may precipitate opioid withdrawal [see Warnings and Precautions (5.3), Adverse Reactions (6)].

Administration Instructions

Instruct patients and their family members or caregivers to:

- Ensure KLOXXADO is present and readily available in locations where a person may be intentionally or accidentally exposed to an opioid overdose (i.e., opioid emergencies).
- Administer KLOXXADO as quickly as possible if a patient is unresponsive and an opioid overdose is suspected, even when in doubt, because prolonged respiratory depression may result in damage to the central nervous system or death. KLOXXADO is not a substitute for emergency medical care [see Dosage and Administration (2.1)].
- Lay the patient on their back and administer KLOXXADO into one nostril while providing support to the back of the neck to allow the head to tilt back [see Dosage and Administration (2.1)].
- Use each nasal spray only one time, DO NOT test or prime prior to use [see Dosage and Administration (2.1)].
- Place patient in a recovery position by turning him/her to their side as shown in the Instructions for Use and
  call for emergency medical assistance immediately after administration of the first dose of KLOXXADO. Additional supportive and/or resuscitative measures may be helpful while awaiting emergency medical
  assistance [see Dosage and Administration (2.1)].
- Monitor patients and administer additional dose of KLOXXADO using a new KLOXXADO every 2 to 3 minutes, if the patient is not responding or responds and then relapses back into respiratory depression. Administer KLOXXADO in alternate nostrils with each dose [see Dosage and Administration (2.1)].
- Replace KLOXXADO before its expiration date.

Distributed by: Hikma

Specialty USA Inc.

Columbus, OH 43228

C50001066/03

Revised September 2025

KLOXXADO® is a registered trademark of Hikma Pharmaceuticals USA Inc.

PATIENT INFORMATION

KLOXXADO® (Kloks-AH-doh)

(naloxone hydrochloride)

nasal spray

You and your family members or caregivers should read this Patient Information leaflet before an opioid emergency happens. This information does not take the place of talking with your healthcare provider about your medical condition or your treatment.

What is the most important information I should know about KLOXXADO nasal spray?

KLOXXADO nasal spray is used to temporarily reverse the effects of opioid medicines. The medicine in KLOXXADO nasal spray has no effect in people who are not taking opioid medicines. Always carry KLOXXADO nasal spray with you in case of an opioid emergency.

- Use KLOXXADO nasal spray right away if you or your caregiver think signs or symptoms of an opioid emergency are present, even if you are not sure, because an opioid emergency can cause severe injury or death. Signs and symptoms of an opioid emergency may include:
  - unusual sleepiness and you are not able to awaken the person with a loud voice or by rubbing firmly on the middle of their chest (sternum)
  - breathing problems including slow or shallow breathing in someone difficult to awaken or who looks like they are not breathing
  - the black circle in the center of the colored part of the eye (pupil) is very small, sometimes called “pinpoint pupils”, in someone difficult to awaken
- Family members, caregivers, or other people who may have to use KLOXXADO nasal spray in an opioid emergency should know where KLOXXADO nasal spray is stored and how to give KLOXXADO nasal spray before an opioid emergency happens.
- Get emergency medical help right away after giving the first dose of KLOXXADO nasal spray. Rescue breathing or CPR (cardiopulmonary resuscitation) may be given while waiting for emergency medical help.
- The signs and symptoms of an opioid emergency can return after KLOXXADO nasal spray is given. If this happens, give another dose after 2 to 3 minutes using a new KLOXXADO nasal spray and watch the person closely until emergency help is received.

What is KLOXXADO nasal spray?

- KLOXXADO nasal spray is a prescription medicine used in adults and children for the treatment of an opioid emergency such as an overdose or a possible opioid overdose with signs of breathing problems and severe sleepiness or not being able to respond.
- KLOXXADO nasal spray is to be given right away and does not take the place of emergency medical care.
- Get emergency medical help right away after giving the first dose of KLOXXADO nasal spray, even if the person wakes up.
- KLOXXADO nasal spray is safe and effective in children for known or suspected opioid overdose.

Do not use KLOXXADO nasal spray if you are allergic to naloxone hydrochloride or any of the ingredients in KLOXXADO nasal spray. See the end of this leaflet for a complete list of ingredients in KLOXXADO nasal spray.

Before using KLOXXADO nasal spray, tell your healthcare provider about all of your medical conditions, including if you:

- have heart problems
- are pregnant or plan to become pregnant. Use of KLOXXADO nasal spray may cause withdrawal symptoms in your unborn baby. Your unborn baby should be examined by a healthcare provider right away after you use KLOXXADO nasal spray.
- are breastfeeding or plan to breastfeed. It is not known if KLOXXADO nasal spray passes into your breast milk.

Tell your healthcare provider about the medicines you take, including prescription and over-the-counter medicines, vitamins, and herbal supplements.

How should I use KLOXXADO nasal spray?

Read the “Instructions for Use” at the end of this Patient Information leaflet for detailed information about the right way to use KLOXXADO nasal spray.

- Use KLOXXADO nasal spray exactly as prescribed by your healthcare provider.
- Each KLOXXADO nasal spray contains only 1 dose of medicine and cannot be reused.
- Lay the person on their back. Support their neck with your hand and allow the head to tilt back before giving KLOXXADO nasal spray.
- KLOXXADO nasal spray should be given into one nostril.
- If additional doses are needed, give KLOXXADO nasal spray in the other nostril.

What are the possible side effects of KLOXXADO nasal spray?

KLOXXADO nasal spray may cause serious side effects, including:

- Sudden opioid withdrawal symptoms. In someone who has been using opioids regularly, opioid withdrawal symptoms can happen suddenly after receiving KLOXXADO nasal spray and may include:

- body aches
- diarrhea
- increased heart rate
- fever
- runny nose
- sneezing

- goose bumps
- sweating
- yawning
- nausea or vomiting
- nervousness

- restlessness or irritability
- shivering or trembling
- stomach cramping
- weakness
- increased blood pressure

In infants under 4 weeks old who have been receiving opioids regularly, sudden opioid withdrawal may be life-threatening if not treated the right way. Signs and symptoms include: seizures, crying more than usual, and
increased reflexes.

The most common side effects of KLOXXADO in adults include: stomach-area (abdomen) pain, weakness, dizziness, headache, nose (nasal) discomfort and a feeling like you are going to faint.

These are not all of the possible side effects of KLOXXADO nasal spray.

Call your doctor for medical advice about side effects. You may report side effects to FDA at 1-800-FDA-1088.

How should I store KLOXXADO nasal spray?

- Store KLOXXADO nasal spray at room temperature between 68ºF to 77ºF (20°C to 25°C).
- Do not freeze. Do not expose to temperatures below 41°F (5°C) or above 104°F (40°C).
- Keep KLOXXADO nasal spray in its box until ready to use. Protect from light.
- Replace KLOXXADO nasal spray before the expiration date on the box.

Keep KLOXXADO nasal spray and all medicines out of the reach of children.

General information about the safe and effective use of KLOXXADO nasal spray.

Medicines are sometimes prescribed for purposes other than those listed in a Patient Information leaflet. Do not use KLOXXADO nasal spray for a condition for which it was not prescribed. You can ask your pharmacist or healthcare provider for information about KLOXXADO nasal spray that is written for health professionals.

What are the ingredients in KLOXXADO nasal spray?

Active ingredient: naloxone hydrochloride

Inactive ingredients: dehydrated alcohol (8 mg strength: 20% (w/w)), edetate disodium dihydrate, propylene glycol, and sodium hydroxide and hydrochloric acid as pH adjusters in purified water.

KLOXXADO nasal spray is not made with natural rubber latex.

Distributed by: Hikma Specialty USA Inc.
Columbus, OH 43228

C50001066/03

KLOXXADO® nasal spray is a registered trademark of Hikma Pharmaceuticals USA Inc.

For more information, visit www.Hikma.com or call Hikma Specialty USA Inc. at 1-800-962-8364.

This Patient Information has been approved by the U.S. Food and Drug Administration. Revised: September 2025

INSTRUCTIONS FOR USE

KLOXXADO® (Kloks-AH-doh)

(naloxone hydrochloride)

nasal spray

You and your family members or caregivers should read the Instructions for Use that comes with KLOXXADO nasal spray before using it. Talk to your healthcare provider if you and your family members or caregivers have any questions about the use of KLOXXADO nasal spray.

Use KLOXXADO nasal spray for known or suspected opioid overdose in adults and children.

Important: For use in the nose only.

- Do not remove or test the KLOXXADO nasal spray until ready to use.
- Each KLOXXADO nasal spray has 1 dose and cannot be reused.
- You do not need to prime KLOXXADO nasal spray.

How to use KLOXXADO nasal spray:

Step 1. Lay the person on their back to receive a dose of KLOXXADO nasal spray.
Step 2. Remove KLOXXADO nasal spray from the box.
  Peel back the tab with the black triangle (▲) to open the
  KLOXXADO nasal spray blister.

Note: KLOXXADO freezes at temperatures below 5°F (-15°C). If this
happens, the device will not spray. Get emergency medical help right
away if this happens. Do not wait for KLOXXADO to thaw. KLOXXADO
may still be used if it has been thawed after being previously frozen.

Step 3. Hold the KLOXXADO nasal spray with your thumb on the bottom of the plunger and your first and middle fingers on either side of the nozzle.
  - Do not apply any pressure until you are ready
    to give the dose.
Step 4. Tilt the person’s head back and provide support under the neck with your hand.
Gentlyinsert the tip of the nozzle into one nostril until
  your fingers on either side of the nozzle are against the bottom of the person’s nose.
Step 5. Press the plunger firmly to give the dose of KLOXXADO
  nasal spray.
Step 6. Remove the KLOXXADO nasal spray from the nostril
  after giving the dose.
What to do after KLOXXADO nasal spray has been used:
Step 7. Get emergency help right away.
15. Move the person on their side (recovery position) after giving KLOXXADO nasal spray.
16. Watch the person closely for 2 to 3 minutes.
17. If the person does not respond by waking up, to voice
  or touch, or start breathing normally, another dose may
  be given.
18. Repeat Steps 2 through 6 using a new KLOXXADO nasal spray to give another dose in the other nostril.
If additional KLOXXADO nasal sprays are available, Steps 2 through 6 may be repeated every 2 to 3 minutes, alternating nostrils, until the person responds or emergency medical help is received.
Step 8.Put the used KLOXXADO nasal spray back into its box.
Step 9. Throw away (dispose of) the used KLOXXADO nasal spray in a place that is away from children.

How should I store KLOXXADO nasal spray?

- Store KLOXXADO nasal spray at room temperature between 68ºF to 77ºF (20°C to 25°C).
- Do not freeze. Do not expose to temperatures below 41°F (5°C) or above 104°F (40°C).
- Keep KLOXXADO nasal spray in its box until ready to use. Protect from light.
- Replace KLOXXADO nasal spray before the expiration date on the box.
Keep KLOXXADO nasal spray and all medicines out of the reach of children.

Distributed by: Hikma Specialty USA Inc.
Columbus, OH 43228

C50001066/03

KLOXXADO® is a registered trademark of Hikma Pharmaceuticals USA Inc.

For more information, visit www.Hikma.com or call Hikma Specialty USA Inc. at 1-800-962-8364.

This Instructions for Use has been approved by the U.S. Food and Drug Administration. Revised: September 2025

PACKAGE/LABEL PRINCIPAL DISPLAY PANEL

KLOXXADO® (naloxone HCl) nasal spray, 8 mg - Folding Carton

NDC # 59467-679-01

PACKAGE/LABEL PRINCIPAL DISPLAY PANEL

KLOXXADO® (naloxone HCl) nasal spray, 8 mg – Foil Peel Backing

NDC # 59467-679-01

PACKAGE/LABEL PRINCIPAL DISPLAY PANEL

KLOXXADO® (naloxone HCl) nasal spray, 8 mg – Device Label - Front

NDC # 59467-679-01

PACKAGE/LABEL PRINCIPAL DISPLAY PANEL

KLOXXADO® (naloxone HCl) nasal spray, 8 mg – Device Label – Back

NDC # 59467-679-01